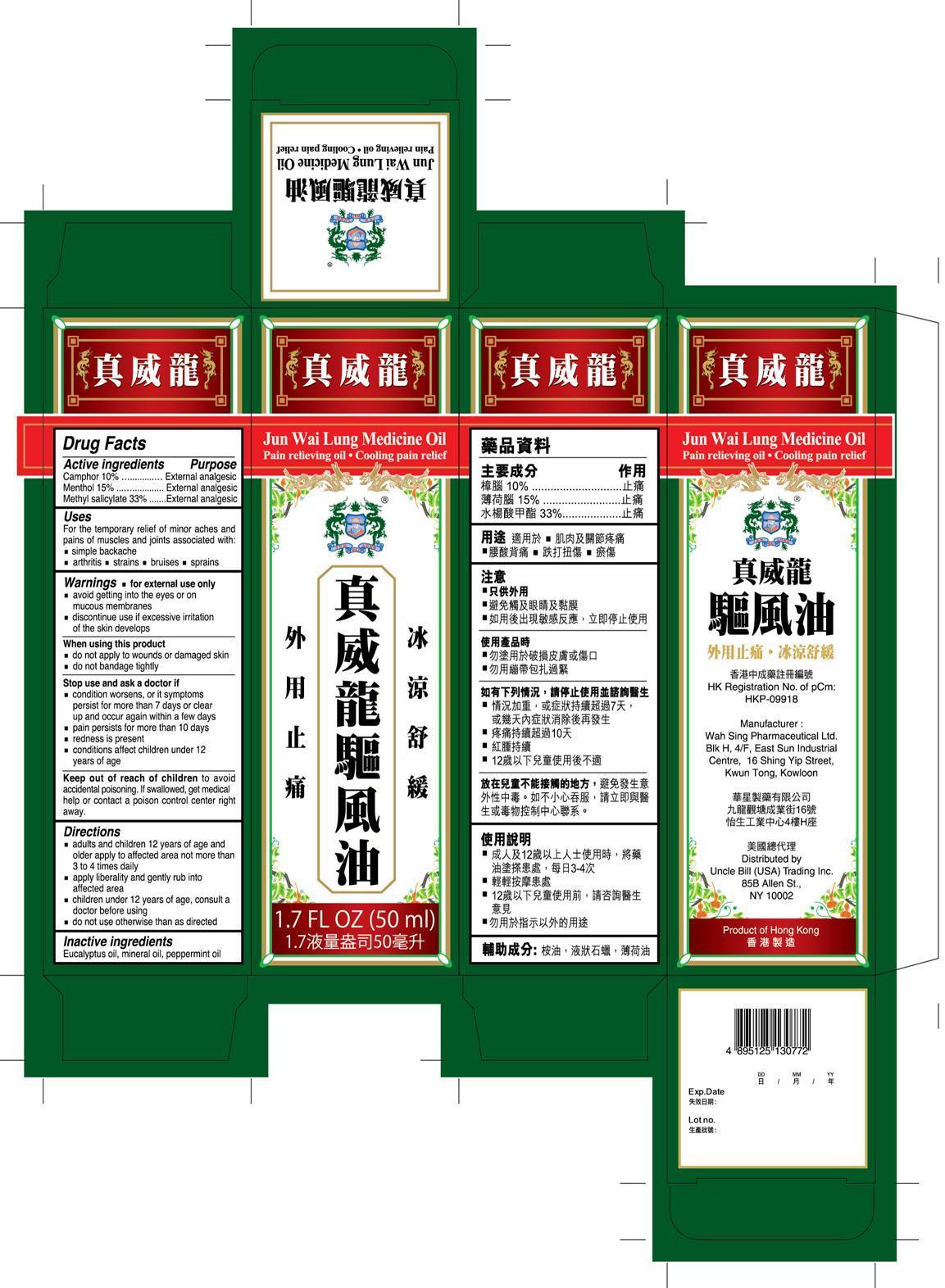 DRUG LABEL: Jun Wai Lung Medicine
NDC: 49952-002 | Form: OIL
Manufacturer: Uncle Bill Trading USA Inc.
Category: otc | Type: HUMAN OTC DRUG LABEL
Date: 20131121

ACTIVE INGREDIENTS: CAMPHOR (SYNTHETIC) 10 g/100 mL; MENTHOL 15 g/100 mL; METHYL SALICYLATE 33 g/100 mL
INACTIVE INGREDIENTS: EUCALYPTUS OIL; MINERAL OIL; PEPPERMINT OIL

Drug Facts

Active Ingredients

Camphor 10%

Menthol 15%

Methyl Salicylate 33%

Purpose

External analgesic

External analgesic

External analgesic

Uses

For the temporary relief of minor aches and pains of muscles and joints associated with:

■ simple backache ■ arthritis ■ strains ■ bruises ■ sprains

Warnings

■ for external use only

■ avoid getting into the eyes or on mucous membranes

■ discontinue use if excessive irritation of the skin develops

When using this product

■ do not apply to wound or damaged skin.

■ do not bandage tightly

Stop use and ask a doctor if

■ condition worsens, or if symptoms persist for more than 7 days or clear up and occur again within a few days

■ pain persists for more than 10 days conditions

■ redness is present

■ conditions affect children under 12 years of age

Keep out of reach of children

to avoid accidental poisoning. If swallowed, get medical help or contact a poison control center right away.

Directions

■ adults and children 12 years of age and older apply to affected area not more than 3 to 4 time daily

■ apply liberally and gently rub into affected area

■ children under 12 years of age, consult a doctor before using

■ do not use otherwise than as directed

Inactive ingredients

Eucalyptus oil, mineral oil, peppermint oil